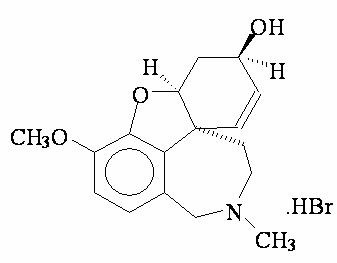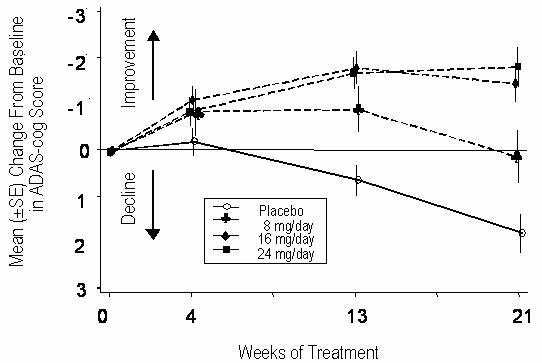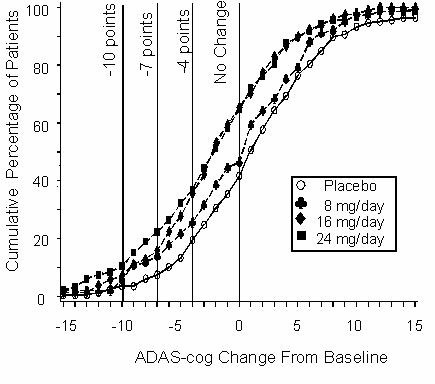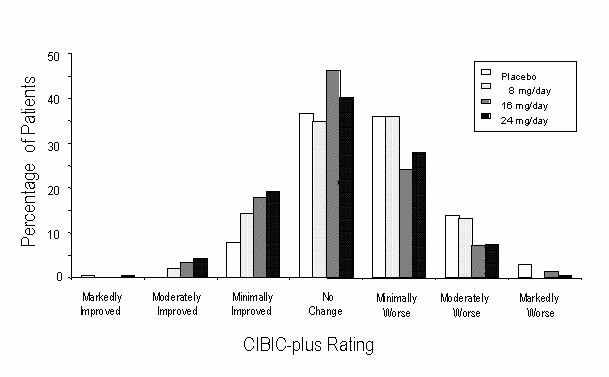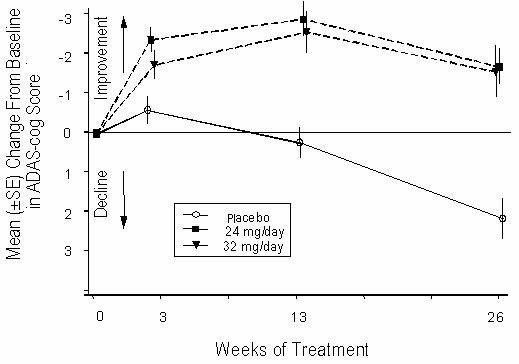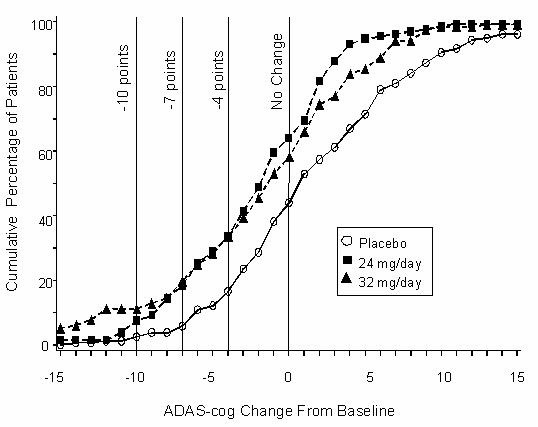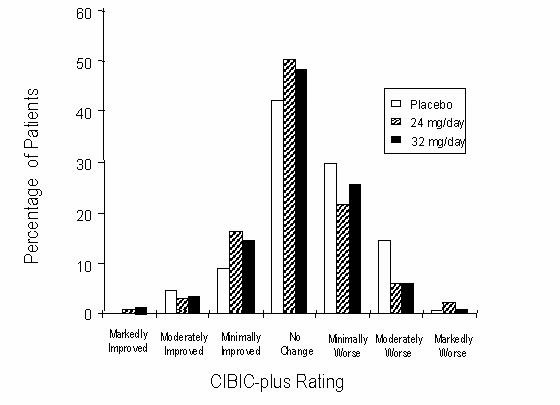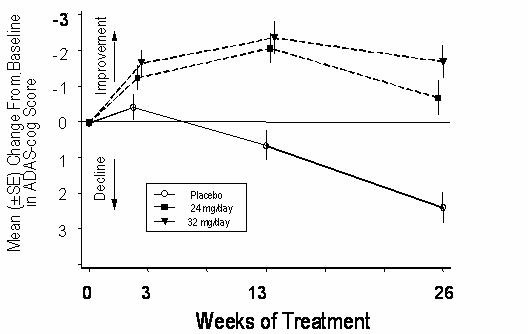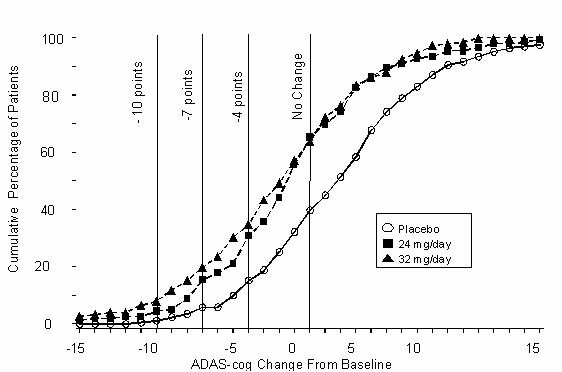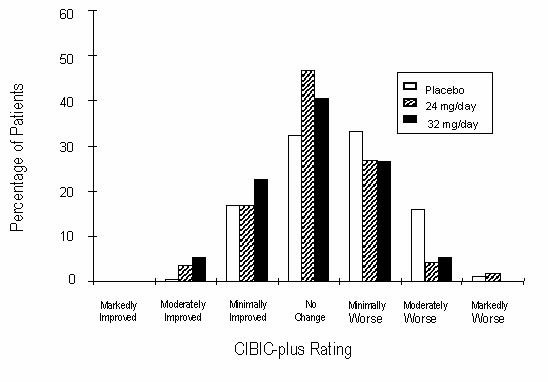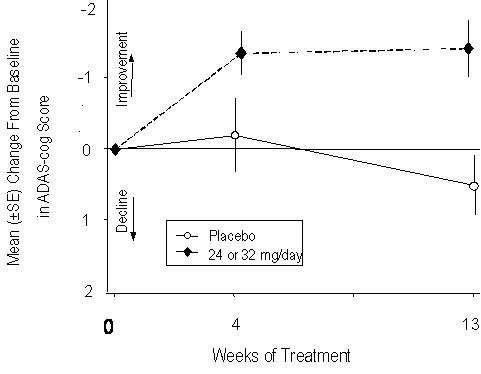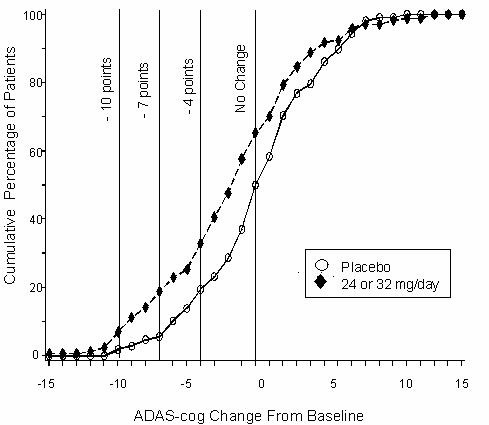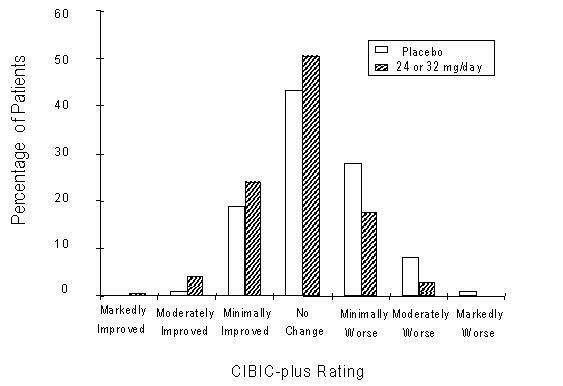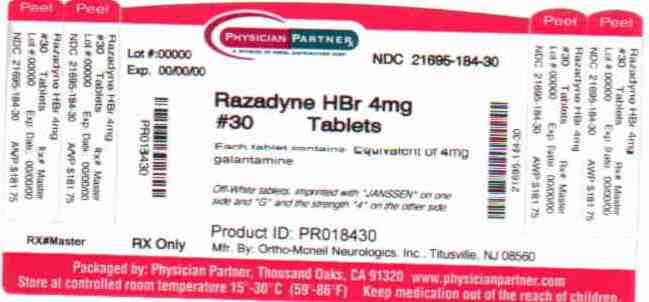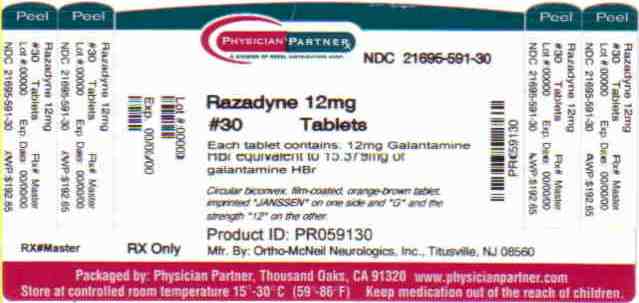 DRUG LABEL: RAZADYNE
NDC: 21695-184 | Form: TABLET, FILM COATED
Manufacturer: Rebel Distributors Corp
Category: prescription | Type: HUMAN PRESCRIPTION DRUG LABEL
Date: 20101111

ACTIVE INGREDIENTS: galantamine hydrobromide 8 mg/1 1
INACTIVE INGREDIENTS: SILICON DIOXIDE; CROSPOVIDONE; HYPROMELLOSES; lactose monohydrate; magnesium stearate; CELLULOSE, MICROCRYSTALLINE; propylene glycol; talc; titanium dioxide; FERRIC OXIDE RED

RAZADYNE®
galantamine HBr
TABLETS

DESCRIPTION

RAZADYNE® ER/RAZADYNE® (galantamine hydrobromide) is galantamine hydrobromide, a reversible, competitive acetylcholinesterase inhibitor. Galantamine hydrobromide is known chemically as (4aS ,6R,8aS)-4a,5,9,10,11,12-hexahydro-3-methoxy-11-methyl-6H -benzofuro[3a,3,2-ef][2]benzazepin-6-ol hydrobromide. It has an empirical formula of C17H21NO3 •HBr and a molecular weight of 368.27. Galantamine hydrobromide is a white to almost white powder and is sparingly soluble in water. The structural formula for galantamine hydrobromide is:

RAZADYNE® ER is available in opaque hard gelatin extended-release capsules of 8 mg (white), 16 mg (pink), and 24 mg (caramel) containing galantamine hydrobromide, equivalent to respectively 8, 16 and 24 mg galantamine base. Inactive ingredients include gelatin, diethyl phthalate, ethylcellulose, hypromellose, polyethylene glycol, titanium dioxide and sugar spheres (sucrose and starch). The 16 mg capsule also contains red ferric oxide. The 24 mg capsule also contains red ferric oxide and yellow ferric oxide.

RAZADYNE® for oral use is available in circular biconvex film-coated immediate-release tablets of 4 mg (off-white), 8 mg (pink), and 12 mg (orange-brown). Each 4, 8, and 12 mg (base equivalent) tablet contains 5.126, 10.253, and 15.379 mg of galantamine hydrobromide, respectively. Inactive ingredients include colloidal silicon dioxide, crospovidone, hypromellose, lactose monohydrate, magnesium stearate, microcrystalline cellulose, propylene glycol, talc, and titanium dioxide. The 4 mg tablets contain yellow ferric oxide. The 8 mg tablets contain red ferric oxide. The 12 mg tablets contain red ferric oxide and FD&C yellow #6 aluminum lake.

RAZADYNE® is also available as a 4 mg/mL oral solution. The inactive ingredients for this solution are methyl parahydroxybenzoate, propyl parahydroxybenzoate, sodium saccharin, sodium hydroxide and purified water.

CLINICAL PHARMACOLOGY

Mechanism of Action

Although the etiology of cognitive impairment in Alzheimer's disease (AD) is not fully understood, it has been reported that acetylcholine-producing neurons degenerate in the brains of patients with Alzheimer's disease. The degree of this cholinergic loss has been correlated with degree of cognitive impairment and density of amyloid plaques (a neuropathological hallmark of Alzheimer's disease).

Galantamine, a tertiary alkaloid, is a competitive and reversible inhibitor of acetylcholinesterase. While the precise mechanism of galantamine's action is unknown, it is postulated to exert its therapeutic effect by enhancing cholinergic function. This is accomplished by increasing the concentration of acetylcholine through reversible inhibition of its hydrolysis by cholinesterase. If this mechanism is correct, galantamine's effect may lessen as the disease process advances and fewer cholinergic neurons remain functionally intact. There is no evidence that galantamine alters the course of the underlying dementing process.

Pharmacokinetics

Galantamine is well absorbed with absolute oral bioavailability of about 90%. It has a terminal elimination half-life of about 7 hours and pharmacokinetics are linear over the range of 8-32 mg/day.

The maximum inhibition of acetylcholinesterase activity of about 40% was achieved about one hour after a single oral dose of 8 mg galantamine in healthy male subjects.

Absorption and Distribution

Galantamine is rapidly and completely absorbed with time to peak concentration about 1 hour. Bioavailability of the tablet was the same as the bioavailability of an oral solution. Food did not affect the AUC of galantamine but Cmax decreased by 25% and Tmax was delayed by 1.5 hours. The mean volume of distribution of galantamine is 175 L.

The plasma protein binding of galantamine is 18% at therapeutically relevant concentrations. In whole blood, galantamine is mainly distributed to blood cells (52.7%). The blood to plasma concentration ratio of galantamine is 1.2.

Metabolism and Elimination

Galantamine is metabolized by hepatic cytochrome P450 enzymes, glucuronidated, and excreted unchanged in the urine. In vitro studies indicate that cytochrome CYP2D6 and CYP3A4 were the major cytochrome P450 isoenzymes involved in the metabolism of galantamine, and inhibitors of both pathways increase oral bioavailability of galantamine modestly (see PRECAUTIONS, Drug-Drug Interactions). O-demethylation, mediated by CYP2D6 was greater in extensive metabolizers of CYP2D6 than in poor metabolizers. In plasma from both poor and extensive metabolizers, however, unchanged galantamine and its glucuronide accounted for most of the sample radioactivity.

In studies of oral ^3H-galantamine, unchanged galantamine and its glucuronide, accounted for most plasma radioactivity in poor and extensive CYP2D6 metabolizers. Up to 8 hours post-dose, unchanged galantamine accounted for 39-77% of the total radioactivity in the plasma, and galantamine glucuronide for 14-24%. By 7 days, 93-99% of the radioactivity had been recovered, with about 95% in urine and about 5% in the feces. Total urinary recovery of unchanged galantamine accounted for, on average, 32% of the dose and that of galantamine glucuronide for another 12% on average.

After i.v. or oral administration, about 20% of the dose was excreted as unchanged galantamine in the urine in 24 hours, representing a renal clearance of about 65 mL/min, about 20-25% of the total plasma clearance of about 300 mL/min.

RAZADYNE® ER 24 mg Extended-Release Capsules administered once daily under fasting conditions are bioequivalent to RAZADYNE® Tablets 12 mg twice daily with respect to AUC24h and Cmin. The Cmax and Tmax of the extended-release capsules were lower and occurred later, respectively, compared with the immediate-release tablets, with Cmax about 25% lower and median Tmax occurring about 4.5 – 5.0 hours after dosing. Dose-proportionality is observed for RAZADYNE® ER Extended-Release Capsules over the dose range of 8 to 24 mg daily and steady state is achieved within a week. There was no effect of age on the pharmacokinetics of RAZADYNE® ER Extended-Release Capsules. CYP2D6 poor metabolizers had drug exposures that were approximately 50% higher than for extensive metabolizers.

There are no appreciable differences in pharmacokinetic parameters when RAZADYNE® ER Extended-Release Capsules are given with food compared to when they are given in the fasted state.

Special Populations

CYP2D6 Poor Metabolizers

Approximately 7% of the normal population has a genetic variation that leads to reduced levels of activity of CYP2D6 isozyme. Such individuals have been referred to as poor metabolizers. After a single oral dose of 4 mg or 8 mg galantamine, CYP2D6 poor metabolizers demonstrated a similar Cmax and about 35% AUC∞ increase of unchanged galantamine compared to extensive metabolizers.

A total of 356 patients with Alzheimer's disease enrolled in two Phase 3 studies were genotyped with respect to CYP2D6 (n=210 hetero-extensive metabolizers, 126 homo-extensive metabolizers, and 20 poor metabolizers). Population pharmacokinetic analysis indicated that there was a 25% decrease in median clearance in poor metabolizers compared to extensive metabolizers. Dosage adjustment is not necessary in patients identified as poor metabolizers as the dose of drug is individually titrated to tolerability.

Hepatic Impairment:

Following a single 4 mg dose of galantamine tablets, the pharmacokinetics of galantamine in subjects with mild hepatic impairment (n=8; Child-Pugh score of 5-6) were similar to those in healthy subjects. In patients with moderate hepatic impairment (n=8; Child-Pugh score of 7-9), galantamine clearance was decreased by about 25% compared to normal volunteers. Exposure would be expected to increase further with increasing degree of hepatic impairment (see PRECAUTIONS and DOSAGE AND ADMINISTRATION).

Renal Impairment:

Following a single 8 mg dose of galantamine tablets, AUC increased by 37% and 67% in moderate and severely renal-impaired patients compared to normal volunteers (see PRECAUTIONS and DOSAGE AND ADMINISTRATION).

Elderly:

Data from clinical trials in patients with Alzheimer's disease indicate that galantamine concentrations are 30-40% higher than in healthy young subjects.

Gender and Race:

No specific pharmacokinetic study was conducted to investigate the effect of gender and race on the disposition of RAZADYNE®, but a population pharmacokinetic analysis indicates (n= 539 males and 550 females) that galantamine clearance is about 20% lower in females than in males (explained by lower body weight in females) and race (n= 1029 White, 24 Black, 13 Asian and 23 other) did not affect the clearance of RAZADYNE®.

Drug-Drug Interactions

(see also PRECAUTIONS, Drug-Drug Interactions)

Multiple metabolic pathways and renal excretion are involved in the elimination of galantamine so no single pathway appears predominant. Based on in vitro studies, CYP2D6 and CYP3A4 were the major enzymes involved in the metabolism of galantamine. CYP2D6 was involved in the formation of O-desmethyl-galantamine, whereas CYP3A4 mediated the formation of galantamine-N-oxide. Galantamine is also glucuronidated and excreted unchanged in urine.

(A) Effect of Other Drugs on the Metabolism of RAZADYNE®:

Drugs that are potent inhibitors for CYP2D6 or CYP3A4 may increase the AUC of galantamine. Multiple dose pharmacokinetic studies demonstrated that the AUC of galantamine increased 30% and 40%, respectively, during coadministration of ketoconazole and paroxetine. As co-administered with erythromycin, another CYP3A4 inhibitor, the galantamine AUC increased only 10%. Population PK analysis with a database of 852 patients with Alzheimer's disease showed that the clearance of galantamine was decreased about 25-33% by concurrent administration of amitriptyline (n = 17), fluoxetine (n = 48), fluvoxamine (n = 14), and quinidine (n = 7), known inhibitors of CYP2D6.

Concurrent administration of H2-antagonists demonstrated that ranitidine did not affect the pharmacokinetics of galantamine, and cimetidine increased the galantamine AUC by approximately 16%.

A multiple dose pharmacokinetic study with concurrent administration of memantine, an N-methyl-D-aspartate (NMDA) receptor antagonist, demonstrated that co-administration of memantine in a dose of 10 mg BID did not affect the pharmacokinetic profile of galantamine (16 mg daily) at steady state.

(B) Effect of RAZADYNE® on the Metabolism of Other Drugs:

In vitro studies show that galantamine did not inhibit the metabolic pathways catalyzed by CYP1A2, CYP2A6, CYP3A4, CYP4A, CYP2C, CYP2D6 and CYP2E1. This indicated that the inhibitory potential of galantamine towards the major forms of cytochrome P450 is very low. Multiple doses of galantamine (24 mg/day) had no effect on the pharmacokinetics of digoxin and warfarin (R- and S- forms). Galantamine had no effect on the increased prothrombin time induced by warfarin.

CLINICAL TRIALS

The effectiveness of RAZADYNE® ER/RAZADYNE® (galantamine hydrobromide) as a treatment for Alzheimer's disease is demonstrated by the results of 5 randomized, double-blind, placebo-controlled clinical investigations in patients with probable Alzheimer's disease, 4 with the immediate-release tablet and 1 with the extended-release capsule [diagnosed by NINCDS-ADRDA criteria, with Mini-Mental State Examination scores that were≥ 10 and ≤ 24]. Doses studied with the tablet formulation were 8-32 mg/day given as twice daily doses. In 3 of the 4 studies with the tablet, patients were started on a low dose of 8 mg, then titrated weekly by 8 mg/day to 24 or 32 mg as assigned. In the fourth study (USA 4-week Dose-Escalation Fixed-Dose Study) dose escalation of 8 mg/day occurred over 4 week intervals. The mean age of patients participating in these 4 RAZADYNE® trials was 75 years with a range of 41 to 100. Approximately 62% of patients were women and 38% were men. The racial distribution was White 94%, Black 3% and other races 3%. Two other studies examined a three times daily dosing regimen; these also showed or suggested benefit but did not suggest an advantage over twice daily dosing.

Study Outcome Measures:

In each study, the primary effectiveness of RAZADYNE® was evaluated using a dual outcome assessment strategy as measured by the Alzheimer's Disease Assessment Scale (ADAS-cog) and the Clinician's Interview Based Impression of Change that required the use of caregiver information (CIBIC-plus).

The ability of RAZADYNE® to improve cognitive performance was assessed with the cognitive sub-scale of the Alzheimer's Disease Assessment Scale (ADAS-cog), a multi-item instrument that has been extensively validated in longitudinal cohorts of Alzheimer's disease patients. The ADAS-cog examines selected aspects of cognitive performance including elements of memory, orientation, attention, reasoning, language and praxis. The ADAS-cog scoring range is from 0 to 70, with higher scores indicating greater cognitive impairment. Elderly normal adults may score as low as 0 or 1, but it is not unusual for non-demented adults to score slightly higher.

The patients recruited as participants in each study using the tablet formulation had mean scores on ADAS-cog of approximately 27 units, with a range from 5 to 69. Experience gained in longitudinal studies of ambulatory patients with mild to moderate Alzheimer's disease suggests that they gain 6 to 12 units a year on the ADAS-cog. Lesser degrees of change, however, are seen in patients with very mild or very advanced disease because the ADAS-cog is not uniformly sensitive to change over the course of the disease. The annualized rate of decline in the placebo patients participating in RAZADYNE® trials was approximately 4.5 units per year.

The ability of RAZADYNE® to produce an overall clinical effect was assessed using a Clinician's Interview Based Impression of Change that required the use of caregiver information, the CIBIC-plus. The CIBIC-plus is not a single instrument and is not a standardized instrument like the ADAS-cog. Clinical trials for investigational drugs have used a variety of CIBIC formats, each different in terms of depth and structure. As such, results from a CIBIC-plus reflect clinical experience from the trial or trials in which it was used and cannot be compared directly with the results of CIBIC-plus evaluations from other clinical trials. The CIBIC-plus used in the trials was a semi-structured instrument based on a comprehensive evaluation at baseline and subsequent time-points of 4 major areas of patient function: general, cognitive, behavioral and activities of daily living. It represents the assessment of a skilled clinician based on his/her observation at an interview with the patient, in combination with information supplied by a caregiver familiar with the behavior of the patient over the interval rated. The CIBIC-plus is scored as a seven point categorical rating, ranging from a score of 1, indicating “markedly improved,” to a score of 4, indicating “no change” to a score of 7, indicating “marked worsening.” The CIBIC-plus has not been systematically compared directly to assessments not using information from caregivers (CIBIC) or other global methods.

Immediate-Release Tablets

U.S. Twenty-One Week Fixed-Dose Study

In a study of 21 weeks duration, 978 patients were randomized to doses of 8, 16, or 24 mg of RAZADYNE® per day, or to placebo, each given in 2 divided doses. Treatment was initiated at 8 mg/day for all patients randomized to RAZADYNE®, and increased by 8 mg/day every 4 weeks. Therefore, the maximum titration phase was 8 weeks and the minimum maintenance phase was 13 weeks (in patients randomized to 24 mg/day of RAZADYNE®).

Effects on the ADAS-cog:

Figure 1 illustrates the time course for the change from baseline in ADAS-cog scores for all four dose groups over the 21 weeks of the study. At 21 weeks of treatment, the mean differences in the ADAS-cog change scores for the RAZADYNE®-treated patients compared to the patients on placebo were 1.7, 3.3, and 3.6 units for the 8, 16 and 24 mg/day treatments, respectively. The 16 mg/day and 24 mg/day treatments were statistically significantly superior to placebo and to the 8 mg/day treatment. There was no statistically significant difference between the 16 mg/day and 24 mg/day dose groups.

Figure 1: Time-Course of the Change From Baseline in ADAS-cog Score for Patients Completing 21 Weeks (5 Months) of Treatment

Figure 2 illustrates the cumulative percentages of patients from each of the four treatment groups who had attained at least the measure of improvement in ADAS-cog score shown on the X-axis. Three change scores (10-point, 7-point and 4-point reductions) and no change in score from baseline have been identified for illustrative purposes, and the percent of patients in each group achieving that result is shown in the inset table.

The curves demonstrate that both patients assigned to galantamine and placebo have a wide range of responses, but that the RAZADYNE® groups are more likely to show the greater improvements.

Figure 2: Cumulative Percentage of Patients Completing 21 Weeks of Double-Blind Treatment With Specified Changes From Baseline in ADAS-cog Scores. The Percentages of Randomized Patients Who Completed the Study Were: Placebo 84%, 8 mg/day 77%, 16 mg/day 78% and 24 mg/day 78%.

 | Change in ADAS-cog
Treatment | -10 | -7 | -4 | 0
Placebo | 3.6% | 7.6% | 19.6% | 41.8%
8 mg/day | 5.9% | 13.9% | 25.7% | 46.5%
16 mg/day | 7.2% | 15.9% | 35.6% | 65.4%
24 mg/day | 10.4% | 22.3% | 37.0% | 64.9%

Effects on the CIBIC-plus:

Figure 3 is a histogram of the percentage distribution of CIBIC-plus scores attained by patients assigned to each of the four treatment groups who completed 21 weeks of treatment. The RAZADYNE®-placebo differences for these groups of patients in mean rating were 0.15, 0.41 and 0.44 units for the 8, 16 and 24 mg/day treatments, respectively. The 16 mg/day and 24 mg/day treatments were statistically significantly superior to placebo. The differences vs. the 8 mg/day treatment for the 16 and 24 mg/day treatments were 0.26 and 0.29, respectively. There were no statistically significant differences between the 16 mg/day and 24 mg/day dose groups.

Figure 3: Distribution of CIBIC-plus Ratings at Week 21

U.S. Twenty-Six Week Fixed-Dose Study

In a study of 26 weeks duration, 636 patients were randomized to either a dose of 24 mg or 32 mg of RAZADYNE® (galantamine hydrobromide) per day, or to placebo, each given in two divided doses. The 26-week study was divided into a 3-week dose titration phase and a 23-week maintenance phase.

Effects on the ADAS-cog:

Figure 4 illustrates the time course for the change from baseline in ADAS-cog scores for all three dose groups over the 26 weeks of the study. At 26 weeks of treatment, the mean differences in the ADAS-cog change scores for the RAZADYNE®-treated patients compared to the patients on placebo were 3.9 and 3.8 units for the 24 mg/day and 32 mg/day treatments, respectively. Both treatments were statistically significantly superior to placebo, but were not significantly different from each other.

Figure 4: Time-Course of the Change From Baseline in ADAS-cog Score for Patients Completing 26 Weeks of Treatment

Figure 5 illustrates the cumulative percentages of patients from each of the three treatment groups who had attained at least the measure of improvement in ADAS-cog score shown on the X-axis. Three change scores (10-point, 7-point and 4-point reductions) and no change in score from baseline have been identified for illustrative purposes, and the percent of patients in each group achieving that result is shown in the inset table.

The curves demonstrate that both patients assigned to RAZADYNE® and placebo have a wide range of responses, but that the RAZADYNE® groups are more likely to show the greater improvements. A curve for an effective treatment would be shifted to the left of the curve for placebo, while an ineffective or deleterious treatment would be superimposed upon, or shifted to the right of the curve for placebo, respectively.

Figure 5: Cumulative Percentage of Patients Completing 26 Weeks of Double-Blind Treatment With Specified Changes From Baseline in ADAS-cog Scores. The Percentages of Randomized Patients Who Completed the Study Were: Placebo 81%, 24 mg/day 68%, and 32 mg/day 58%.

 | Change in ADAS-cog
Treatment | -10 | -7 | -4 | 0
Placebo | 2.1% | 5.7% | 16.6% | 43.9%
24 mg/day | 7.6% | 18.3% | 33.6% | 64.1%
32 mg/day | 11.1% | 19.7% | 33.3% | 58.1%

Effects on the CIBIC-plus:

Figure 6 is a histogram of the percentage distribution of CIBIC-plus scores attained by patients assigned to each of the three treatment groups who completed 26 weeks of treatment. The mean RAZADYNE®-placebo differences for these groups of patients in the mean rating were 0.28 and 0.29 units for 24 and 32 mg/day of RAZADYNE®, respectively. The mean ratings for both groups were statistically significantly superior to placebo, but were not significantly different from each other.

Figure 6: Distribution of CIBIC-plus Ratings at Week 26

International Twenty-Six Week Fixed-Dose Study

In a study of 26 weeks duration identical in design to the USA 26-Week Fixed-Dose Study, 653 patients were randomized to either a dose of 24 mg or 32 mg of RAZADYNE® per day, or to placebo, each given in two divided doses. The 26-week study was divided into a 3-week dose titration phase and a 23-week maintenance phase.

Effects on the ADAS-cog:

Figure 7 illustrates the time course for the change from baseline in ADAS-cog scores for all three dose groups over the 26 weeks of the study. At 26 weeks of treatment, the mean differences in the ADAS-cog change scores for the RAZADYNE®-treated patients compared to the patients on placebo were 3.1 and 4.1 units for the 24 mg/day and 32 mg/day treatments, respectively. Both treatments were statistically significantly superior to placebo, but were not significantly different from each other.

Figure 7: Time-Course of the Change From Baseline in ADAS-cog Score for Patients Completing 26 Weeks of Treatment

Figure 8 illustrates the cumulative percentages of patients from each of the three treatment groups who had attained at least the measure of improvement in ADAS-cog score shown on the X-axis. Three change scores (10-point, 7-point and 4-point reductions) and no change in score from baseline have been identified for illustrative purposes, and the percent of patients in each group achieving that result is shown in the inset table.

The curves demonstrate that both patients assigned to RAZADYNE® and placebo have a wide range of responses, but that the RAZADYNE® groups are more likely to show the greater improvements.

Figure 8: Cumulative Percentage of Patients Completing 26 Weeks of Double-Blind Treatment With Specified Changes From Baseline in ADAS-cog Scores. The Percentages of Randomized Patients Who Completed the Study Were: Placebo 87%, 24 mg/day 80%, and 32 mg/day 75%.

 | Change in ADAS-cog
Treatment | -10 | -7 | -4 | 0
Placebo | 1.2% | 5.8% | 15.2% | 39.8%
24 mg/day | 4.5% | 15.4% | 30.8% | 65.4%
32 mg/day | 7.9% | 19.7% | 34.9% | 63.8%

Effects on the CIBIC-plus:

Figure 9 is a histogram of the percentage distribution of CIBIC-plus scores attained by patients assigned to each of the three treatment groups who completed 26 weeks of treatment. The mean RAZADYNE®-placebo differences for these groups of patients in the mean rating of change from baseline were 0.34 and 0.47 for 24 and 32 mg/day of RAZADYNE®, respectively. The mean ratings for the RAZADYNE® groups were statistically significantly superior to placebo, but were not significantly different from each other.

Figure 9: Distribution of CIBIC-plus Rating at Week 26

International Thirteen-Week Flexible-Dose Study

In a study of 13 weeks duration, 386 patients were randomized to either a flexible dose of 24-32 mg/day of RAZADYNE® or to placebo, each given in two divided doses. The 13-week study was divided into a 3-week dose titration phase and a 10-week maintenance phase. The patients in the active treatment arm of the study were maintained at either 24 mg/day or 32 mg/day at the discretion of the investigator.

Effects on the ADAS-cog:

Figure 10 illustrates the time course for the change from baseline in ADAS-cog scores for both dose groups over the 13 weeks of the study. At 13 weeks of treatment, the mean difference in the ADAS-cog change scores for the treated patients compared to the patients on placebo was 1.9. RAZADYNE® at a dose of 24-32 mg/day was statistically significantly superior to placebo.

Figure 10: Time-Course of the Change From Baseline in ADAS-cog Score for Patients Completing 13 Weeks of Treatment

Figure 11 illustrates the cumulative percentages of patients from each ofthe two treatment groups who had attained at least the measure of improvement in ADAS-cog score shown on the X-axis. Three change scores (10-point, 7-point and 4-point reductions) and no change in score from baseline have been identified for illustrative purposes, and the percent of patients in each group achieving that result is shown in the inset table.

The curves demonstrate that both patients assigned to RAZADYNE® and placebo have a wide range of responses, but that the RAZADYNE® group is more likely to show the greater improvement.

Figure 11: Cumulative Percentage of Patients Completing 13 Weeks of Double-Blind Treatment With Specified Changes from Baseline in ADAS-cog Scores. The Percentages of Randomized Patients Who Completed the Study Were: Placebo 90%, 24-32 mg/day 67%.

 | Change in ADAS-cog
Treatment | -10 | -7 | -4 | 0
Placebo | 1.9% | 5.6% | 19.4% | 50.0%
24 or 32 mg/day | 7.1% | 18.8% | 32.9% | 65.3%

Effects on the CIBIC-plus:

Figure 12 is a histogram of the percentage distribution of CIBIC-plus scores attained by patients assigned to each of the two treatment groups who completed 13 weeks of treatment. The mean RAZADYNE®-placebo differences for the group of patients in the mean rating of change from baseline were 0.37 units. The mean rating for the 24-32 mg/day group was statistically significantly superior to placebo.

Figure 12: Distribution of CIBIC-plus Ratings at Week 13

Age, Gender and Race:

Patient's age, gender, or race did not predict clinical outcome of treatment.

Extended-Release Capsules

The efficacy of RAZADYNE® ER Extended-Release Capsules was studied in a randomized, double-blind, placebo-controlled trial which was 6 months in duration, and had an initial 4-week dose-escalation phase. In this trial, patients were assigned to one of 3 treatment groups: RAZADYNE® ER in a flexible dose of 16 to 24 mg once daily; RAZADYNE® Tablets in a flexible dose of 8 to 12 mg twice daily; and placebo. The primary efficacy measures in this study were the ADAS-cog and CIBIC-plus. On the protocol-specified primary efficacy analysis at Month 6, a statistically significant improvement favoring RAZADYNE® ER over placebo was seen for the ADAS-cog, but not for the CIBIC-plus. RAZADYNE® ER showed a statistically significant improvement when compared with placebo on the Alzheimer's Disease Cooperative Study-Activities of Daily Living (ADCS-ADL) scale, a measure of function, and a secondary efficacy measure in this study. The effects of both RAZADYNE® ER Capsules and RAZADYNE® Tablets on the ADAS-cog, CIBIC-plus, and ADCS-ADL were similar in this study.

INDICATIONS AND USAGE

RAZADYNE® ER/RAZADYNE® (galantamine hydrobromide) is indicated for the treatment of mild to moderate dementia of the Alzheimer's type.

CONTRAINDICATIONS

RAZADYNE® ER/RAZADYNE® (galantamine hydrobromide) is contraindicated in patients with known hypersensitivity to galantamine hydrobromide or to any excipients used in the formulation.

WARNINGS

Anesthesia

Galantamine, as a cholinesterase inhibitor, is likely to exaggerate the neuromuscular blocking effects of succinylcholine-type and similar neuromuscular blocking agents during anesthesia.

Cardiovascular Conditions

Because of their pharmacological action, cholinesterase inhibitors have vagotonic effects on the sinoatrial and atrioventricular nodes, leading to bradycardia and AV block. These actions may be particularly important to patients with supraventricular cardiac conduction disorders or to patients taking other drugs concomitantly that significantly slow heart rate. Postmarketing surveillance of marketed anticholinesterase inhibitors has shown, however, that bradycardia and all types of heart block have been reported in patients both with and without known underlying cardiac conduction abnormalities. Therefore all patients should be considered at risk for adverse effects on cardiac conduction.

In randomized controlled trials, bradycardia was reported more frequently in galantamine-treated patients than in placebo-treated patients, but was rarely severe and rarely led to treatment discontinuation. The overall frequency of this event was 2-3% for galantamine doses up to 24 mg/day compared with <1% for placebo. No increased incidence of heart block was observed at the recommended doses.

Patients treated with galantamine up to 24 mg/day using the recommended dosing schedule showed a dose-related increase in risk of syncope (placebo 0.7% [2/286]; 4 mg BID 0.4% [3/692]; 8 mg BID 1.3% [7/552]; 12 mg BID 2.2% [6/273]).

Gastrointestinal Conditions

Through their primary action, cholinomimetics may be expected to increase gastric acid secretion due to increased cholinergic activity. Therefore, patients should be monitored closely for symptoms of active or occult gastrointestinal bleeding, especially those with an increased risk for developing ulcers, e.g., those with a history of ulcer disease or patients using concurrent nonsteroidal anti-inflammatory drugs (NSAIDS). Clinical studies of RAZADYNE® (galantamine hydrobromide) have shown no increase, relative to placebo, in the incidence of either peptic ulcer disease or gastrointestinal bleeding.

RAZADYNE® ER/RAZADYNE®, as a predictable consequence of its pharmacological properties, has been shown to produce nausea, vomiting, diarrhea, anorexia, and weight loss (see ADVERSE REACTIONS).

Genitourinary

Although this was not observed in clinical trials with RAZADYNE® ER/RAZADYNE®, cholinomimetics may cause bladder outflow obstruction.

Neurological Conditions

Seizures: Cholinesterase inhibitors are believed to have some potential to cause generalized convulsions. However, seizure activity may also be a manifestation of Alzheimer's disease. In clinical trials, there was no increase in the incidence of convulsions with RAZADYNE® ER/RAZADYNE®, compared to placebo.

Pulmonary Conditions

Because of its cholinomimetic action, galantamine should be prescribed with care to patients with a history of severe asthma or obstructive pulmonary disease.

PRECAUTIONS

Information for Patients and Caregivers:

Caregivers should be instructed about the recommended dosage and administration of RAZADYNE® ER/RAZADYNE® (galantamine hydrobromide). RAZADYNE® ER Extended-Release Capsules should be administered once daily in the morning, preferably with food (although not required). RAZADYNE® Tablets and Oral Solution should be administered twice per day, preferably with the morning and evening meals. Dose escalation (dose increases) should follow a minimum of four weeks at prior dose.

Patients and caregivers should be advised that the most frequent adverse events associated with use of the drug can be minimized by following the recommended dosage and administration.

Patients and caregivers should be advised to ensure adequate fluid intake during treatment. If therapy has been interrupted for several days or longer, the patient should be restarted at the lowest dose and the dose escalated to the current dose.

Caregivers should be instructed in the correct procedure for administering RAZADYNE® Oral Solution. In addition, they should be informed of the existence of an Instruction Sheet (included with the product) describing how the solution is to be administered. They should be urged to read this sheet prior to administering RAZADYNE® Oral Solution. Caregivers should direct questions about the administration of the solution to either their physician or pharmacist.

Deaths in Subjects with Mild Cognitive Impairment (MCI)

In two randomized placebo controlled trials of 2 years duration in subjects with mild cognitive impairment (MCI), a total of 13 subjects on RAZADYNE® (n=1026) and 1 subject on placebo (n=1022) died. The deaths were due to various causes which could be expected in an elderly population; about half of the RAZADYNE® deaths appeared to result from various vascular causes (myocardial infarction, stroke, and sudden death).

Although the difference in mortality between RAZADYNE® and placebo-treated groups in these two studies was significant, the results are highly discrepant with other studies of RAZADYNE®. Specifically, in these two MCI studies, the mortality rate in the placebo-treated subjects was markedly lower than the rate in placebo-treated patients in trials of RAZADYNE® in Alzheimer's disease or other dementias (0.7 per 1000 person years compared to 22-61 per 1000 person years, respectively). Although the mortality rate in the RAZADYNE®-treated MCI subjects was also lower than that observed in RAZADYNE®-treated patients in Alzheimer's disease and other dementia trials (10.2 per 1000 person years compared to 23-31 per 1000 person years, respectively), the relative difference was much less. When the Alzheimer's disease and other dementia studies were pooled (n=6000), the mortality rate in the placebo group numerically exceeded that in the RAZADYNE® group. Furthermore, in the MCI studies, no subjects in the placebo group died after 6 months, a highly unexpected finding in this population.

Individuals with mild cognitive impairment demonstrate isolated memory impairment greater than expected for their age and education, but do not meet current diagnostic criteria for Alzheimer's disease.

Special Populations

Hepatic Impairment

In patients with moderately impaired hepatic function, dose titration should proceed cautiously (see CLINICAL PHARMACOLOGY and DOSAGE AND ADMINISTRATION). The use of RAZADYNE® in patients with severe hepatic impairment is not recommended.

Renal Impairment

In patients with moderately impaired renal function, dose titration should proceed cautiously (see CLINICAL PHARMACOLOGY and DOSAGE AND ADMINISTRATION). In patients with severely impaired renal function (CLcr < 9 mL/min) the use of RAZADYNE® is not recommended.

Drug-Drug Interactions

(see also CLINICAL PHARMACOLOGY, Drug-Drug Interactions)

Use With Anticholinergics

RAZADYNE® has the potential to interfere with the activity of anticholinergic medications.

Use With Cholinomimetics and Other Cholinesterase Inhibitors

A synergistic effect is expected when cholinesterase inhibitors are given concurrently with succinylcholine, other cholinesterase inhibitors, similar neuromuscular blocking agents or cholinergic agonists such as bethanechol.

A) Effect of Other Drugs on Galantamine

In vitro

CYP3A4 and CYP2D6 are the major enzymes involved in the metabolism of galantamine. CYP3A4 mediates the formation of galantamine-N-oxide; CYP2D6 leads to the formation of O-desmethyl-galantamine. Because galantamine is also glucuronidated and excreted unchanged, no single pathway appears predominant.

In vivo

Cimetidine and Ranitidine: Galantamine was administered as a single dose of 4 mg on day 2 of a 3-day treatment with either cimetidine (800 mg daily) or ranitidine (300 mg daily). Cimetidine increased the bioavailability of galantamine by approximately 16%. Ranitidine had no effect on the PK of galantamine.

Ketoconazole: Ketoconazole, a strong inhibitor of CYP3A4 and an inhibitor of CYP2D6, at a dose of 200 mg BID for 4 days, increased the AUC of galantamine by 30%.

Erythromycin : Erythromycin, a moderate inhibitor of CYP3A4 at a dose of 500 mg QID for 4 days, affected the AUC of galantamine minimally (10% increase).

Paroxetine: Paroxetine, a strong inhibitor of CYP2D6, at 20 mg/day for 16 days, increased the oral bioavailability of galantamine by about 40%.

Memantine: Memantine, an N-methyl-D-aspartate receptor antagonist, at a dose of 10 mg BID, had no effect on the pharmacokinetics of galantamine (16 mg/day) at steady state.

B) Effect of Galantamine on Other Drugs

In vitro

Galantamine did not inhibit the metabolic pathways catalyzed by CYP1A2, CYP2A6, CYP3A4, CYP4A, CYP2C, CYP2D6 or CYP2E1. This indicates that the inhibitory potential of galantamine towards the major forms of cytochrome P450 is very low.

In vivo

Warfarin: Galantamine at 24 mg/day had no effect on the pharmacokinetics of R- and S-warfarin (25 mg single dose) or on the prothrombin time. The protein binding of warfarin was unaffected by galantamine.

Digoxin: Galantamine at 24 mg/day had no effect on the steady-state pharmacokinetics of digoxin (0.375 mg once daily) when they were coadministered. In this study, however, one healthy subject was hospitalized for 2nd and 3rd degree heart block and bradycardia.

Carcinogenesis, Mutagenesis and Impairment of Fertility

In a 24-month oral carcinogenicity study in rats, a slight increase in endometrial adenocarcinomas was observed at 10 mg/kg/day (4 times the Maximum Recommended Human Dose [MRHD] on a mg/m^2 basis or 6 times on an exposure [AUC] basis) and 30 mg/kg/day (12 times MRHD on a mg/m^2 basis or 19 times on an AUC basis). No increase in neoplastic changes was observed in females at 2.5 mg/kg/day (equivalent to the MRHD on a mg/m^2 basis or 2 times on an AUC basis) or in males up to the highest dose tested of 30 mg/kg/day (12 times the MRHD on a mg/m^2 and AUC basis).

Galantamine was not carcinogenic in a 6-month oral carcinogenicity study in transgenic (P 53-deficient) mice up to 20 mg/kg/day, or in a 24-month oral carcinogenicity study in male and female mice up to 10 mg/kg/day (2 times the MRHD on a mg/m^2 basis and equivalent on an AUC basis).

Galantamine produced no evidence of genotoxic potential when evaluated in the in vitro Ames S. typhimurium or E. coli reverse mutation assay, in vitro mouse lymphoma assay, in vivo micronucleus test in mice, or in vitro chromosome aberration assay in Chinese hamster ovary cells.

No impairment of fertility was seen in rats given up to 16 mg/kg/day (7 times the MRHD on a mg/m^2 basis) for 14 days prior to mating in females and for 60 days prior to mating in males.

Pregnancy

Pregnancy Category B: In a study in which rats were dosed from day 14 (females) or day 60 (males) prior to mating through the period of organogenesis, a slightly increased incidence of skeletal variations was observed at doses of 8 mg/kg/day (3 times the Maximum Recommended Human Dose [MRHD] on a mg/m^2 basis) and 16 mg/kg/day. In a study in which pregnant rats were dosed from the beginning of organogenesis through day 21 post-partum, pup weights were decreased at 8 and 16 mg/kg/day, but no adverse effects on other postnatal developmental parameters were seen. The doses causing the above effects in rats produced slight maternal toxicity. No major malformations were caused in rats given up to 16 mg/kg/day. No drug related teratogenic effects were observed in rabbits given up to 40 mg/kg/day (32 times the MRHD on a mg/m^2 basis) during the period of organogenesis.

There are no adequate and well-controlled studies of RAZADYNE® in pregnant women. RAZADYNE® should be used during pregnancy only if the potential benefit justifies the potential risk to the fetus.

Nursing Mothers

It is not known whether galantamine is excreted in human breast milk. RAZADYNE® has no indication for use in nursing mothers.

Pediatric Use

There are no adequate and well-controlled trials documenting the safety and efficacy of galantamine in any illness occurring in children. Therefore, use of RAZADYNE® in children is not recommended.

ADVERSE REACTIONS

Pre-Marketing Clinical Trial Experience:

The specific adverse event data described in this section are based on studies of the immediate-release tablet formulation. In clinical trials, once-daily treatment with RAZADYNE® ER (galantamine hydrobromide) Extended-Release Capsules was well tolerated and adverse events were similar to those seen with RAZADYNE® Tablets.

Adverse Events Leading to Discontinuation:

In two large scale, placebo-controlled trials of 6 months duration in which patients were titrated weekly from 8 to 16 to 24, and to 32 mg/day, the risk of discontinuation because of an adverse event in the galantamine group exceeded that in the placebo group by about threefold. In contrast, in a 5-month trial with escalation of the dose by 8 mg/day every 4 weeks, the overall risk of discontinuation because of an adverse event was 7%, 7%, and 10% for the placebo, galantamine 16 mg/day, and galantamine 24 mg/day groups, respectively, with gastrointestinal adverse effects the principle reason for discontinuing galantamine. Table 1 shows the most frequent adverse events leading to discontinuation in this study.

Table 1: Most Frequent Adverse Events Leading to Discontinuation in a Placebo-Controlled, Double-Blind Trial With a 4-Week Dose Escalation Schedule
4-Week Escalation
 | Placebo | 16 mg/day | 24 mg/day
Adverse Event | N=286 | N=279 | N=273
Nausea | <1% | 2% | 4%
Vomiting | 0% | 1% | 3%
Anorexia | <1% | 1% | <1%
Dizziness | <1% | 2% | 1%
Syncope | 0% | 0% | 1%

Adverse Events Reported in Controlled Trials:

The reported adverse events in trials using RAZADYNE® (galantamine hydrobromide) Tablets reflect experience gained under closely monitored conditions in a highly selected patient population. In actual practice or in other clinical trials, these frequency estimates may not apply, as the conditions of use, reporting behavior and the types of patients treated may differ.

The majority of these adverse events occurred during the dose-escalation period. In those patients who experienced the most frequent adverse event, nausea, the median duration of the nausea was 5-7 days.

Administration of RAZADYNE® with food, the use of anti-emetic medication, and ensuring adequate fluid intake may reduce the impact of these events.

The most frequent adverse events, defined as those occurring at a frequency of at least 5% and at least twice the rate on placebo with the recommended maintenance dose of either 16 or 24 mg/day of RAZADYNE® under conditions of every 4-week dose-escalation for each dose increment of 8 mg/day, are shown in Table 2. These events were primarily gastrointestinal and tended to be less frequent with the 16 mg/day recommended initial maintenance dose.

Table 2: The Most Frequent Adverse Events in the Placebo-Controlled Trial With Dose Escalation Every 4 Weeks Occurring in at Least 5% of Patients Receiving RAZADYNE® and at Least Twice the Rate on Placebo.
 | Placebo | RAZADYNE® 16 mg/day | RAZADYNE® 24 mg/day
Adverse Event | N=286 | N=279 | N=273
Nausea | 5% | 13% | 17%
Vomiting | 1% | 6% | 10%
Diarrhea | 6% | 12% | 6%
Anorexia | 3% | 7% | 9%
Weight decrease | 1% | 5% | 5%

Table 3: The most common adverse events (adverse events occurring with an incidence of at least 2% with RAZADYNE® treatment and in which the incidence was greater than with placebo treatment) are listed in Table 3 for four placebo-controlled trials for patients treated with 16 or 24 mg/day of RAZADYNE®.

Table 3: Adverse Events Reported in at Least 2% of Patients With Alzheimer's Disease Administered RAZADYNE® and at a Frequency Greater Than With Placebo
Body System Adverse Event | Placebo (N=801) | RAZADYNE® [Adverse events in patients treated with 16 or 24 mg/day of RAZADYNE® in four placebo-controlled trials are included.] (N=1040)
Body as a whole - general disorders
Fatigue | 3% | 5%
Syncope | 1% | 2%
Central & peripheral nervous system disorders
Dizziness | 6% | 9%
Headache | 5% | 8%
Tremor | 2% | 3%
Gastrointestinal system disorders
Nausea | 9% | 24%
Vomiting | 4% | 13%
Diarrhea | 7% | 9%
Abdominal pain | 4% | 5%
Dyspepsia | 2% | 5%
Heart rate and rhythm disorders
Bradycardia | 1% | 2%
Metabolic and nutritional disorders
Weight decrease | 2% | 7%
Psychiatric disorders
Anorexia | 3% | 9%
Depression | 5% | 7%
Insomnia | 4% | 5%
Somnolence | 3% | 4%
Red blood cell disorders
Anemia | 2% | 3%
Respiratory system disorders
Rhinitis | 3% | 4%
Urinary system disorders
Urinary tract infection | 7% | 8%
Hematuria | 2% | 3%

Adverse events occurring with an incidence of at least 2% in RAZADYNE-treated patients that was either equal to or greater than with placebo treatment were constipation, agitation, confusion, anxiety, hallucination, injury, back pain, peripheral edema, asthenia, chest pain, urinary incontinence, upper respiratory tract infection, bronchitis, coughing, hypertension, fall, and purpura.

There were no important differences in adverse event rates related to dose or sex. Therewere too few non-Caucasian patients to assess the effects of race on adverse event rates.

No clinically relevant abnormalities in laboratory values were observed.

Other Adverse Events Observed During Clinical Trials

RAZADYNE® Tablets were administered to 3055 patients with Alzheimer's disease. A total of 2357 patients received galantamine in placebo-controlled trials and 761 patients with Alzheimer's disease received galantamine 24 mg/day, the maximum recommended maintenance dose. About 1000 patients received galantamine for at least one year and approximately 200 patients received galantamine for two years.

To establish the rate of adverse events, data from all patients receiving any dose of galantamine in 8 placebo-controlled trials and 6 open-label extension trials were pooled. The methodology to gather and codify these adverse events was standardized across trials, using WHO terminology. All adverse events occurring in approximately 0.1% are included, except for those already listed elsewhere in labeling, WHO terms too general to be informative, or events unlikely to be drug caused. Events are classified by body system and listed using the following definitions: frequent adverse events - those occurring in at least 1/100 patients; infrequent adverse events - those occurring in 1/100 to 1/1000 patients; rare adverse events - those occurring in fewer than 1/1000 patients. These adverse events are not necessarily related to RAZADYNE® treatment and in most cases were observed at a similar frequency in placebo-treated patients in the controlled studies. Additional adverse events observed in other clinical trials are also included below.

Body As a Whole – General Disorders: Frequent: chest pain, asthenia, fever, malaise

Cardiovascular System Disorders: Infrequent: postural hypotension, hypotension, dependent edema, cardiac failure, myocardial ischemia or infarction

Central & Peripheral Nervous System Disorders: Infrequent : vertigo, hypertonia, convulsions, involuntary muscle contractions, paresthesia, ataxia, hypokinesia, hyperkinesia, apraxia, aphasia, leg cramps, tinnitus, transient ischemic attack or cerebrovascular accident

Gastrointestinal System Disorders: Frequent: flatulence; Infrequent: gastritis, melena, dysphagia, rectal hemorrhage, dry mouth, saliva increased, diverticulitis, gastroenteritis, hiccup; Rare: esophageal perforation

Heart Rate & Rhythm Disorders: Infrequent: AV block, palpitation, atrial arrhythmias including atrial fibrillation and supraventricular tachycardia, QT prolonged, bundle branch block, T-wave inversion, ventricular tachycardia; Rare: severe bradycardia

Metabolic& Nutritional Disorders: Infrequent : hyperglycemia, alkaline phosphatase increased

Platelet, Bleeding& Clotting Disorders: Infrequent : purpura, epistaxis, thrombocytopenia

Psychiatric Disorders: Infrequent: apathy, paroniria, paranoid reaction, libido increased, delirium; Rare: suicidal ideation, suicide

Urinary System Disorders: Frequent: incontinence; Infrequent: hematuria, micturition frequency, cystitis, urinary retention, nocturia, renal calculi

Post-Marketing Experience:

Other adverse events from post-approval controlled and uncontrolled clinical trials and post-marketing experience observed in patients treated with RAZADYNE® include:

Body as a Whole – General Disorders: dehydration (including rare, severe cases leading to renal insufficiency and renal failure)

Psychiatric Disorders: aggression

Gastrointestinal System Disorders: upper and lower GI bleeding, stomach discomfort, abdominal discomfort

Hepatobiliary Disorders:elevated liver enzymes, hepatitis

Metabolic& Nutritional Disorders: hypokalemia

Nervous System Disorders: lethargy, dysgeusia, hypersomnia

Eye disorders: vision blurred

These adverse events may or may not be causally related to the drug.

OVERDOSAGE

Because strategies for the management of overdose are continually evolving, it is advisable to contact a poison control center to determine the latest recommendations for the management of an overdose of any drug.

As in any case of overdose, general supportive measures should be utilized. Signs and symptoms of significant overdosing of galantamine are predicted to be similar to those of overdosing of other cholinomimetics. These effects generally involve the central nervous system, the parasympathetic nervous system, and the neuromuscular junction. In addition to muscle weakness or fasciculations, some or all of the following signs of cholinergic crisis may develop: severe nausea, vomiting, gastrointestinal cramping, salivation, lacrimation, urination, defecation, sweating, bradycardia, hypotension, respiratory depression, collapse and convulsions. Increasing muscle weakness is a possibility and may result in death if respiratory muscles are involved.

Tertiary anticholinergics such as atropine may be used as an antidote for RAZADYNE® (galantamine hydrobromide) overdosage. Intravenous atropine sulfate titrated to effect is recommended at an initial dose of 0.5 to 1.0 mg i.v. with subsequent doses based upon clinical response. Atypical responses in blood pressure and heart rate have been reported with other cholinomimetics when coadministered with quaternary anticholinergics. It is not known whether RAZADYNE® and/or its metabolites can be removed by dialysis (hemodialysis, peritoneal dialysis, or hemofiltration). Dose-related signs of toxicity in animals included hypoactivity, tremors, clonic convulsions, salivation, lacrimation, chromodacryorrhea, mucoid feces, and dyspnea.

In one postmarketing report, one patient who had been taking 4 mg of galantamine daily for a week inadvertently ingested eight 4 mg tablets (32 mg total) on a single day. Subsequently, she developed bradycardia, QT prolongation, ventricular tachycardia and torsades de pointes accompanied by a brief loss of consciousness for which she required hospital treatment. Two additional cases of accidental ingestion of 32 mg (nausea, vomiting, and dry mouth; nausea, vomiting, and substernal chest pain) and one of 40 mg (vomiting), resulted in brief hospitalizations for observation with full recovery. One patient who was prescribed 24 mg/day and had a history of hallucinations over the previous two years, mistakenly received 24 mg twice daily for 34 days and developed hallucinations requiring hospitalization. Another patient, who was prescribed 16 mg/day of oral solution, inadvertently ingested 160 mg (40 mL) and experienced sweating, vomiting, bradycardia, and near-syncope one hour later, which necessitated hospital treatment. His symptoms resolved within 24 hours.

DOSAGE AND ADMINISTRATION

RAZADYNE® ER Extended-Release Capsules

The dosage of RAZADYNE® ER (galantamine hydrobromide) Extended-Release Capsules was shown to be effective in a controlled clinical trial is 16-24mg/day.

The recommended starting dose of RAZADYNE® ER is 8 mg/day. The dose should be increased to the initial maintenance dose of 16 mg/day after a minimum of 4 weeks. A further increase to 24 mg/day should be attempted after a minimum of 4 weeks at 16 mg/day. Dose increases should be based upon assessment of clinical benefit and tolerability of the previous dose.

RAZADYNE® ER should be administered once daily in the morning, preferably with food.

Patients currently being treated with RAZADYNE® tablets can convert to RAZADYNE® ER by taking their last dose of RAZADYNE® tablets in the evening and starting RAZADYNE® ER once daily treatment the next morning. Converting from RAZADYNE® to RAZADYNE® ER should occur at the same total daily dose.

RAZADYNE® Immediate-Release Tablets

The dosage of RAZADYNE® Tablets was shown to be effective in controlled clinical trials is 16-32 mg/day given as twice daily dosing. As the dose of 32 mg/day is less well tolerated than lower doses and does not provide increased effectiveness, the recommended dose range is 16-24 mg/day given in a BID regimen. The dose of 24 mg/day did not provide a statistically significant greater clinical benefit than 16 mg/day. It is possible, however, that a daily dose of 24 mg of RAZADYNE® might provide additional benefit for some patients.

The recommended starting dose of RAZADYNE® Tablets and Oral Solution is 4 mg twice a day (8 mg/day). The dose should be increased to the initial maintenance dose of 8 mg twice a day (16 mg/day) after a minimum of 4 weeks. A further increase to 12 mg twice a day (24 mg/day) should be attempted after a minimum of 4 weeks at 8 mg twice a day (16 mg/day). Dose increases should be based upon assessment of clinical benefit and tolerability of the previous dose.

RAZADYNE® Tablets and Oral Solution should be administered twice a day, preferably with morning and evening meals.

Patients and caregivers should be advised to ensure adequate fluid intake during treatment. If therapy has been interrupted for several days or longer, the patient should be restarted at the lowest dose and the dose escalated to the current dose.

Caregivers should be instructed in the correct procedure for administering RAZADYNE® Oral Solution. In addition, they should be informed of the existence of an Instruction Sheet (included with the product) describing how the solution is to be administered. They should be urged to read this sheet prior to administering RAZADYNE® Oral Solution. Caregivers should direct questions about the administration of the solution to either their physician or pharmacist.

The abrupt withdrawal of RAZADYNE® ER/RAZADYNE® in those patients who had been receiving doses in the effective range was not associated with an increased frequency of adverse events in comparison with those continuing to receive the same doses of that drug. The beneficial effects of RAZADYNE® ER/RAZADYNE® are lost, however, when the drug is discontinued.

Doses in Special Populations

Galantamine plasma concentrations may be increased in patients with moderate to severe hepatic impairment. In patients with moderately impaired hepatic function (Child-Pugh score of 7-9), the total daily dose should generally not exceed 16 mg/day. The use of RAZADYNE® ER/RAZADYNE® in patients with severe hepatic impairment (Child-Pugh score of 10-15) is not recommended.

For patients with moderate renal impairment the dose should generally not exceed 16 mg/day. In patients with severe renal impairment (creatinine clearance < 9 mL/min), the use of RAZADYNE® ER/RAZADYNE® is not recommended.

HOW SUPPLIED

RAZADYNE® Tablets are imprinted “JANSSEN” on one side, and “G” and the strength “4”, “8”, or “12” on the other.

4 mg off-white tablet: bottles of 30 NDC 21695-184-30

12 mg orange-brown tablet: bottles of 30 NDC 21695-591-30

Storage and Handling

RAZADYNE® Tablets should be stored at 25°C (77°F); excursions permitted to 15-30°C (59-86°F) [see USP Controlled Room Temperature].

Keep out of reach of children.

RAZADYNE® Tablets are manufactured by:
JOLLC, Gurabo, Puerto Rico 00778

RAZADYNE® Tablets are manufactured for:

Ortho-McNeil Neurologics, Division of Ortho-McNeil-Janssen Pharmaceuticals, Inc.
Titusville, NJ 08560

Repackaged by:

Rebel Distributors Corp

Thousand Oaks, CA 91320

US Patent No. 4,663,318
© Ortho-McNeil-Janssen Pharmaceuticals, Inc.